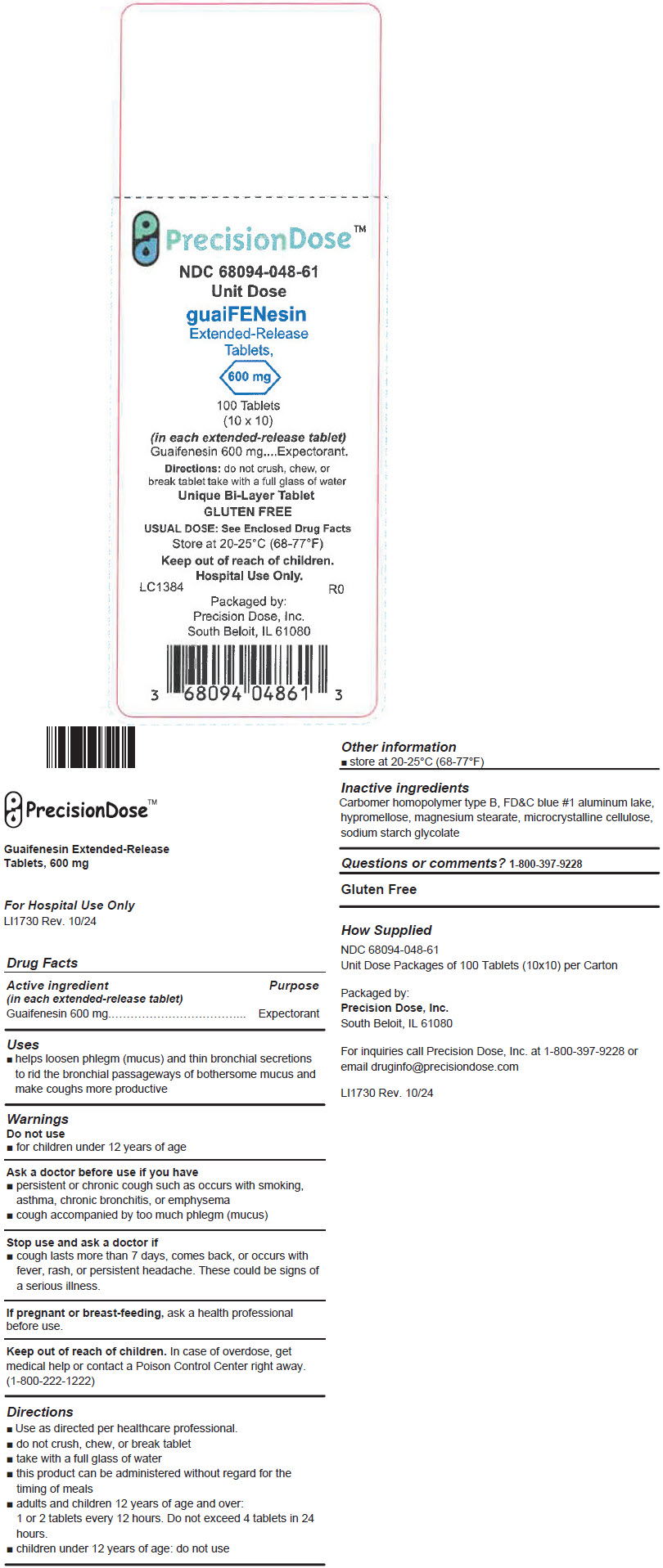 DRUG LABEL: Guaifenesin Extended-Release
NDC: 68094-048 | Form: TABLET, MULTILAYER, EXTENDED RELEASE
Manufacturer: Precision Dose Inc.
Category: otc | Type: HUMAN OTC DRUG LABEL
Date: 20250527

ACTIVE INGREDIENTS: Guaifenesin 600 mg/1 1
INACTIVE INGREDIENTS: CARBOMER HOMOPOLYMER TYPE B (ALLYL PENTAERYTHRITOL OR ALLYL SUCROSE CROSSLINKED); FD&C BLUE NO. 1; HYPROMELLOSE, UNSPECIFIED; MAGNESIUM STEARATE; MICROCRYSTALLINE CELLULOSE

Guaifenesin Extended-Release

Tablets, 600 mg

For Hospital Use Only
LI1730 Rev. 10/24

Drug Facts

Active ingredient (in each extended-release tablet)

Guaifenesin 600 mg

Purpose

Expectorant

Uses

- helps loosen phlegm (mucus) and thin bronchial secretions to rid the bronchial passageways of bothersome mucus and make coughs more productive

Warnings

Do not use

- for children under 12 years of age

Ask a doctor before use if you have

- persistent or chronic cough such as occurs with smoking, asthma, chronic bronchitis, or emphysema
- cough accompanied by too much phlegm (mucus)

Stop use and ask a doctor if

- cough lasts more than 7 days, comes back, or occurs with fever, rash, or persistent headache. These could be signs of a serious illness.

PREGNANCY OR BREAST FEEDING

If pregnant or breast-feeding, ask a health professional before use.

Keep out of reach of children. In case of overdose, get medical help or contact a Poison Control Center right away. (1-800-222-1222)

Directions

- Use as directed per healthcare professional.
- do not crush, chew, or break tablet
- take with a full glass of water
- this product can be administered without regard for the timing of meals
- adults and children 12 years of age and over: 1 or 2 tablets every 12 hours. Do not exceed 4 tablets in 24 hours.
- children under 12 years of age: do not use

Other information

- store at 20-25°C (68-77°F)

Inactive ingredients

Carbomer homopolymer type B, FD&C blue #1 aluminum lake, hypromellose, magnesium stearate, microcrystalline cellulose, sodium starch glycolate

Questions or comments?

1-800-397-9228

Gluten Free

How Supplied

NDC 68094-048-61
Unit Dose Packages of 100 Tablets (10×10) per Carton

Packaged by:
Precision Dose, Inc.
South Beloit, IL 61080

For inquiries call Precision Dose, Inc. at 1-800-397-9228 or email druginfo@precisiondose.com

LI1730 Rev. 10/24

PRINCIPAL DISPLAY PANEL - 600 mg Tablet Blister Pack Carton

PrecisionDose™

NDC 68094-048-61
Unit Dose

guaiFENesin
Extended-Release
Tablets,

600 mg

100 Tablets
(10 x 10)

(in each extended-release tablet)
Guaifenesin 600 mg....Expectorant.

Directions: do not crush, chew, or
break tablet take with a full glass of water

Unique Bi-Layer Tablet
GLUTEN FREE

USUAL DOSE: See Enclosed Drug Facts
Store at 20-25°C (68-77°F)

Keep out of reach of children.
Hospital Use Only.

LC1384
R0

Packaged by:
Precision Dose, Inc.
South Beloit, IL 61080